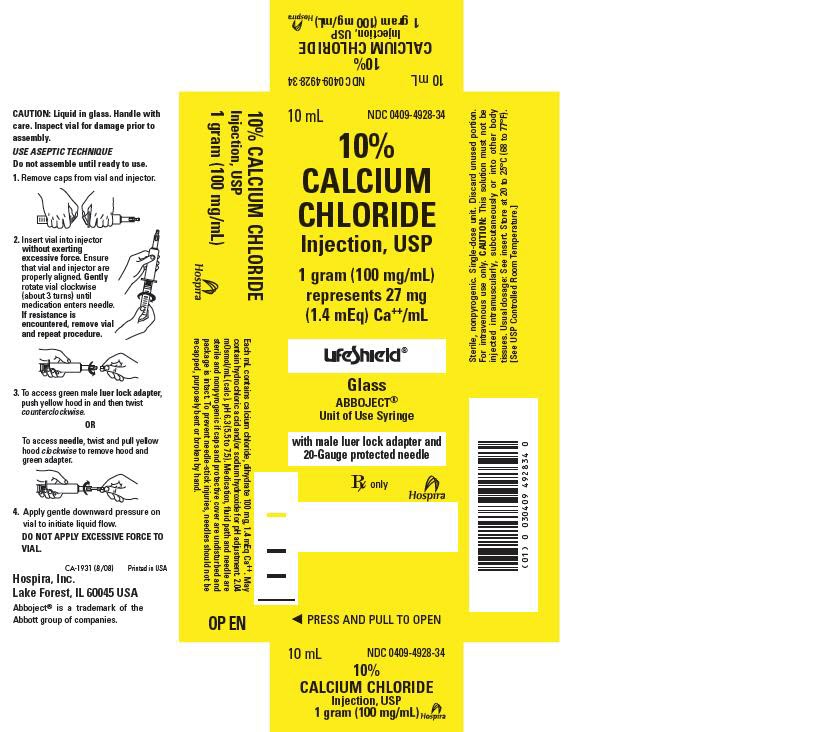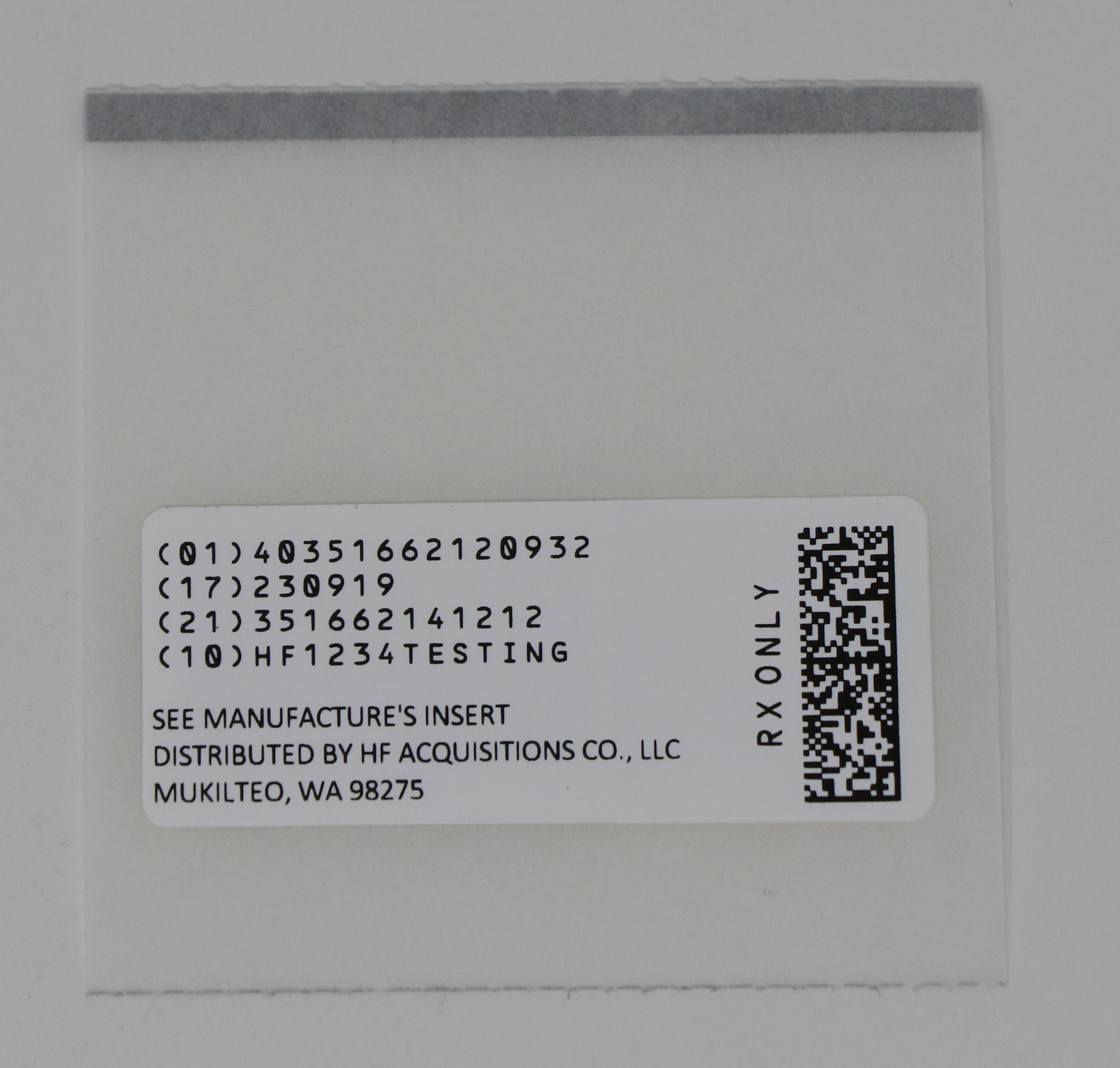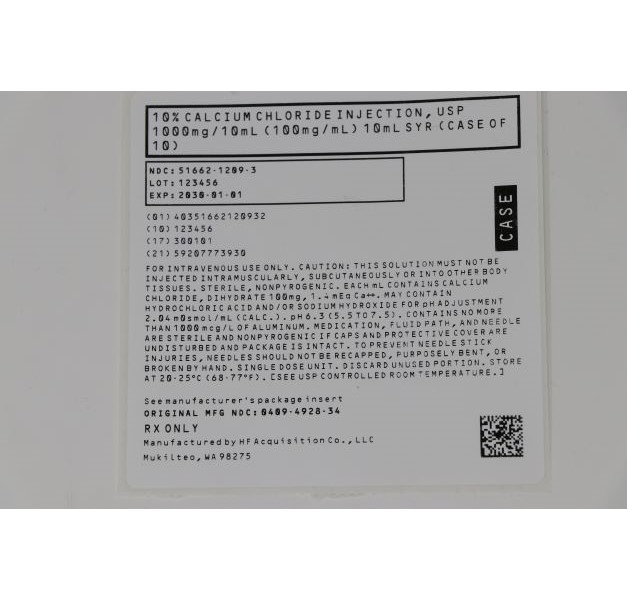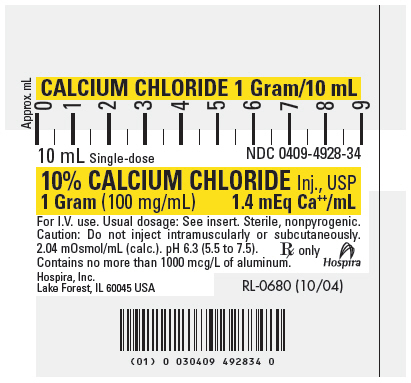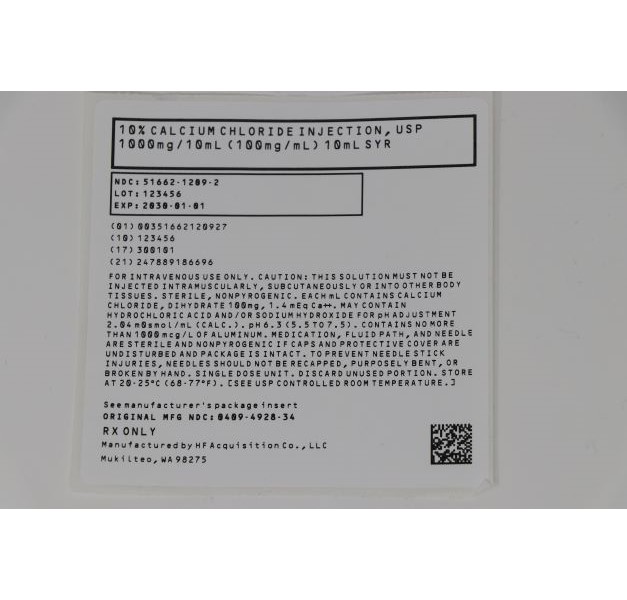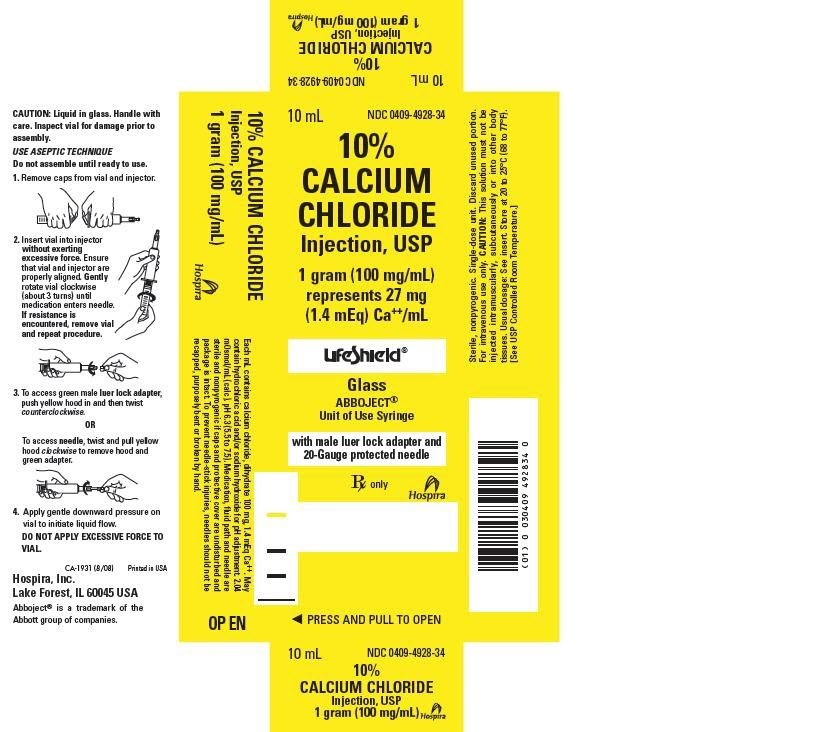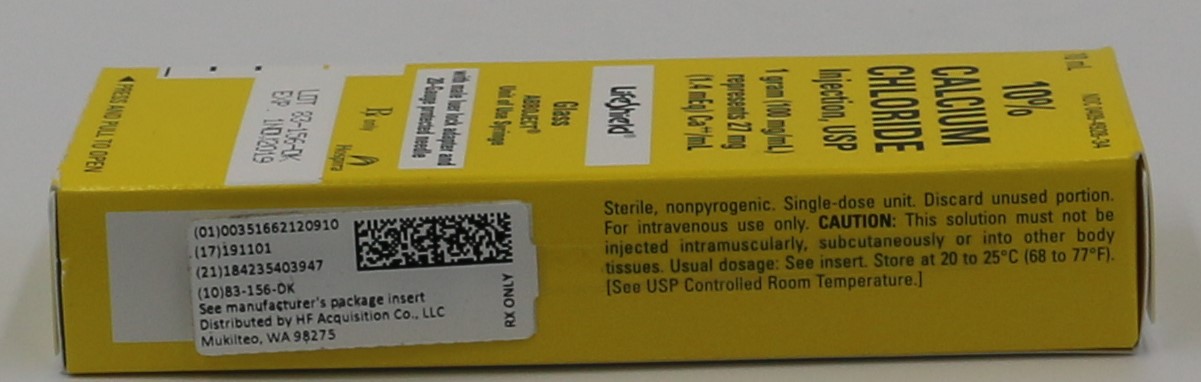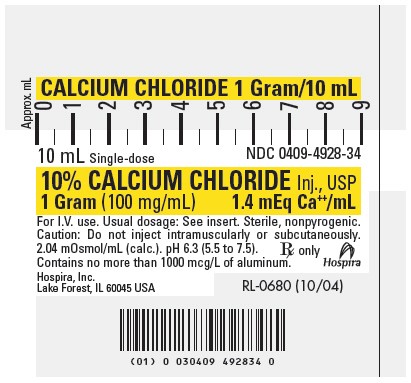 DRUG LABEL: CALCIUM CHLORIDE
NDC: 51662-1209 | Form: INJECTION, SOLUTION
Manufacturer: HF Acquisition Co LLC, DBA HealthFirst
Category: prescription | Type: HUMAN PRESCRIPTION DRUG LABEL
Date: 20240129

ACTIVE INGREDIENTS: CALCIUM CHLORIDE 100 mg/1 mL
INACTIVE INGREDIENTS: WATER; HYDROCHLORIC ACID; SODIUM HYDROXIDE

10% CALCIUM CHLORIDE INJECTION, USP 1gram (100mg/mL) SYR

SPL UNCLASSIFIED

100 mg/mL Rx only
Represents 27 mg (1.4 mEq) Ca++/mL
ABBOJECT® Syringe
A HYPERTONIC SOLUTION IN A 10 ML
UNIT OF USE SYRINGE FOR PROMPT
INTRAVENOUS INJECTION.
CAUTION: This solution must not be injected
intramuscularly or subcutaneously.

DESCRIPTION

10% Calcium Chloride Injection, USP is a sterile, nonpyrogenic, hypertonic solution containing 100 mg (1.4 mEq/mL) of calcium chloride, dihydrate (1.4 mEq each of Ca++ and Cl¯) in water for injection. It is provided in a 10 mL Unit of Use Syringe to facilitate prompt intravenous injection. The solution is administered only by intravenous or intraventricular cavity injection as a calcium replenisher.

The solution contains no bacteriostat, antimicrobial agent or added buffer and is intended only for use as a single-dose injection. As per USP testing, when diluted with water for injection to make a 5% solution, the pH of calcium chloride injection is 6.3 (5.5 to 7.5). May contain hydrochloric acid and/or sodium hydroxide for pH adjustment. The osmolar concentration is 2.04 mOsmol/mL (calc.). 10% Calcium Chloride Injection, USP is oxygen sensitive.

Calcium Chloride, USP dihydrate is chemically designated CaCl2 · 2H2O (dihydrate) white, odorless fragments or granules freely soluble in water.

CLINICAL PHARMACOLOGY

Calcium is the fifth most abundant element in the body and the major fraction is in the bony structure. Calcium plays important physiological roles, many of which are poorly understood. It is essential for the functional integrity of the nervous and muscular systems. It is necessary for normal cardiac function and is one of the factors that operates in the mechanisms involved in the coagulation of blood.

Calcium chloride in water dissociates to provide calcium (Ca++) and chloride (Cl¯) ions. They are normal constituents of the body fluids and are dependent on various physiological mechanisms for maintenance of balance between intake and output. Approximately 80% of body calcium is excreted in the feces as insoluble salts; urinary excretion accounts for the remaining 20%.

INDICATIONS & uSAGE

10% Calcium Chloride Injection, USP is indicated (1) for the treatment of hypocalcemia in those conditions requiring a prompt increase in blood plasma calcium levels, (2) in the treatment of magnesium intoxication due to overdosage of magnesium sulfate and (3) to combat the deleterious effects of hyperkalemia as measured by electrocardiographic (ECG), pending correction of the increased potassium level in the extracellular fluid.

10% Calcium Chloride Injection, USP also may be used in cardiac resuscitation when weak or inadequate contractions return following defibrillation or when epinephrine injection has failed to strengthen myocardial contractions.

CONTRAINDICATIONS

Calcium chloride is contraindicated for cardiac resuscitation in the presence of ventricular fibrillation or in patients with the risk of existing digitalis toxicity.

WARNINGS

10% Calcium Chloride Injection, USP is irritating to veins and must not be injected into tissues, since severe necrosis and sloughing may occur. Great care should be taken to avoid extravasation or accidental injection into perivascular tissues.

WARNING: This product contains aluminum that may be toxic. Aluminum may reach toxic levels with prolonged parenteral administration if kidney function is impaired. Premature neonates are particularly at risk because their kidneys are immature, and they require large amounts of calcium and phosphate solutions, which contain aluminum.

Research indicates that patients with impaired kidney function, including premature neonates, who receive parenteral levels of aluminum at greater than 4 to 5 mcg/kg/day accumulate aluminum at levels associated with central nervous system and bone toxicity. Tissue loading may occur at even lower rates of administration.

PRECAUTIONS

Do not administer unless solution is clear and seal is intact. Discard unused portion.

Because of its additive effect, calcium should be administered very cautiously to a patient who is digitalized or who is taking effective doses of digitalis or digitalis-like preparations.

Injections should be made slowly through a small needle into a large vein to minimize venous irritation and avoid undesirable reactions. It is particularly important to prevent a high concentration of calcium from reaching the heart because of the danger of cardiac syncope. If injected into the ventricular cavity in cardiac resuscitation, it must not be injected into the myocardial tissue.

Pregnancy: Animal reproduction studies have not been conducted with calcium chloride. It also is not known whether calcium chloride can cause fetal harm when administered to a pregnant woman or can affect reproduction capacity. Calcium chloride should be given to a pregnant woman only if clearly needed.

ADVERSE REACTIONS

Rapid injection may cause the patient to complain of tingling sensations, a calcium taste, a sense of oppression or “heat wave”.

Injections of calcium chloride are accompanied by peripheral vasodilatation as well as a local “burning” sensation and there may be a moderate fall in blood pressure.

Should perivascular infiltration occur, I.V. administration at that site should be discontinued at once. Local infiltration of the affected area with 1% procaine hydrochloride, to which hyaluronidase may be added, will often reduce venospasm and dilute the calcium remaining in the tissues locally. Local application of heat may also be helpful.

DRUG ABUSE & DEPENDENCE

None known.

DOSAGE & ADMINISTRATION

10% Calcium Chloride Injection, USP is administered only by slow intravenous injection (not to exceed 1 mL/min) and/or in cardiac resuscitation, by injection into the ventricular cavity. It must not be injected into the myocardium.

The usual precautions for intravenous therapy should be observed. If time permits, the solution should be warmed to body temperature. The injection should be halted if the patient complains of any discomfort; it may be resumed when symptoms disappear. Following injection, the patient should remain recumbent for a short time.

The usual adult dosage in hypocalcemic disorders ranges from 500 mg to 1 g (5 to 10 mL) at intervals of 1 to 3 days, depending on the response of the patient and/or results of serum calcium determinations. Repeated injections may be required because of rapid excretion of calcium.

In magnesium intoxication, an initial adult dose of 500 mg (5 mL) should be administered promptly and the patient observed for signs of recovery before further doses are given.

In hyperkalemic ECG disturbances of cardiac function, the dosage of calcium chloride injection should be titrated by constant monitoring of ECG changes during administration.

In cardiac resuscitation, the usual adult dosage ranges from 500 mg to 1 g (5 to 10 mL) intravenously, or from 200 to 800 mg (2 to 8 mL) when injected into the ventricular cavity.

Parenteral drug products should be inspected visually for particulate matter and discoloration prior to administration, whenever solution and container permit. See PRECAUTIONS.

To prevent needle-stick injuries, needles should not be recapped, purposely bent or broken by hand.

OVERDOSAGE

oo rapid injection may produce lowering of blood pressure and cardiac syncope. Persistent hypercalcemia from overdosage of calcium is unlikely because of rapid excretion. In the event of untoward effects from excessive calcium administration, the drug should be discontinued promptly, the patient re-evaluated and appropriate countermeasures instituted, if necessary. See PRECAUTIONS and ADVERSE REACTIONS.

HOW SUPPLIED

10% CALCIUM CHLORIDE INJECTION is supplied in the following dosage forms.
NDC 51662-1209-1
10% CALCIUM CHLORIDE INJECTION, USP 1gram (100mg/mL) SYR

NDC 51662-1209-2
10% CALCIUM CHLORIDE INJECTION, USP 1gram (100mg/mL) SYR, 1 SYRINGE PER POUCH

NDC 51662-1209-3

10% CALCIUM CHLORIDE INJECTION, USP 1gram (100mg/mL) SYR, 1 SYRINGE PER POUCH, 10 POUCHES PER CASE

HF Acquisition Co LLC, DBA HealthFirst
Mukilteo, WA 98275

Store at 20 to 25°C (68 to 77°F). [See USP Controlled Room Temperature.]

Abboject® is a trademark of the Abbott group of companies

LIFESHIELD® is the trademark of ICU Medical, Inc.

PRINCIPLE DISPLAY PANEL, SYRINGE

CALCIUM CHLORIDE 1 Gram/10 mL

10 mL Single-dose
NDC 0409-4928-34

10% CALCIUM CHLORIDE Inj., USP
1 Gram (100 mg/mL)
1.4 mEq Ca++/mL

For I.V. use. Usual dosage: See insert. Sterile, nonpyrogenic.
Caution: Do not inject intramuscularly or subcutaneously.
2.04 mOsmol/mL (calc.). pH 6.3 (5.5 to 7.5).
Contains no more than 1000 mcg/L of aluminum.

Rx only

Hospira

Hospira, Inc.
Lake Forest, IL 60045 USA

RL-0680 (10/04)

PRINCIPLE DISPLAY PANEL, CARTON

10 mL

NDC 0409-4928-34

10%
CALCIUM
CHLORIDE
Injection, USP

1 gram (100 mg/mL)
represents 27 mg
(1.4 mEq) Ca++/mL

LifeShield®

Glass
ABBOJECT®
Unit of Use Syringe

with male luer lock adapter and
20-Gauge protected needle

Rx only

Hospira

◀ PRESS AND PULL TO OPEN

PRINCIPAL DISPLAY PANEL - NDC 51662-1209-2 POUCH LABELING

NDC 51662-1209-2 POUCH LABELING

CARTON LABELING

SYRINGE LABEL

PRINCIPAL DISPLAY PANEL - NDC 51662-1209-3 CASE LABELING

NDC 51662-1209-2 CASE LABELING

SERIALIZED CASE RFID LABELING